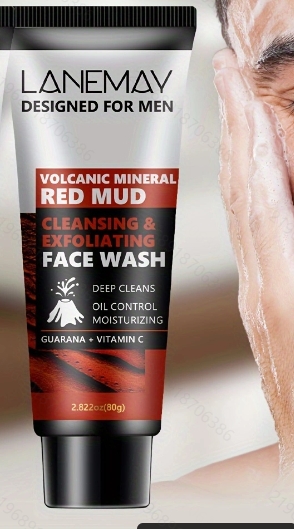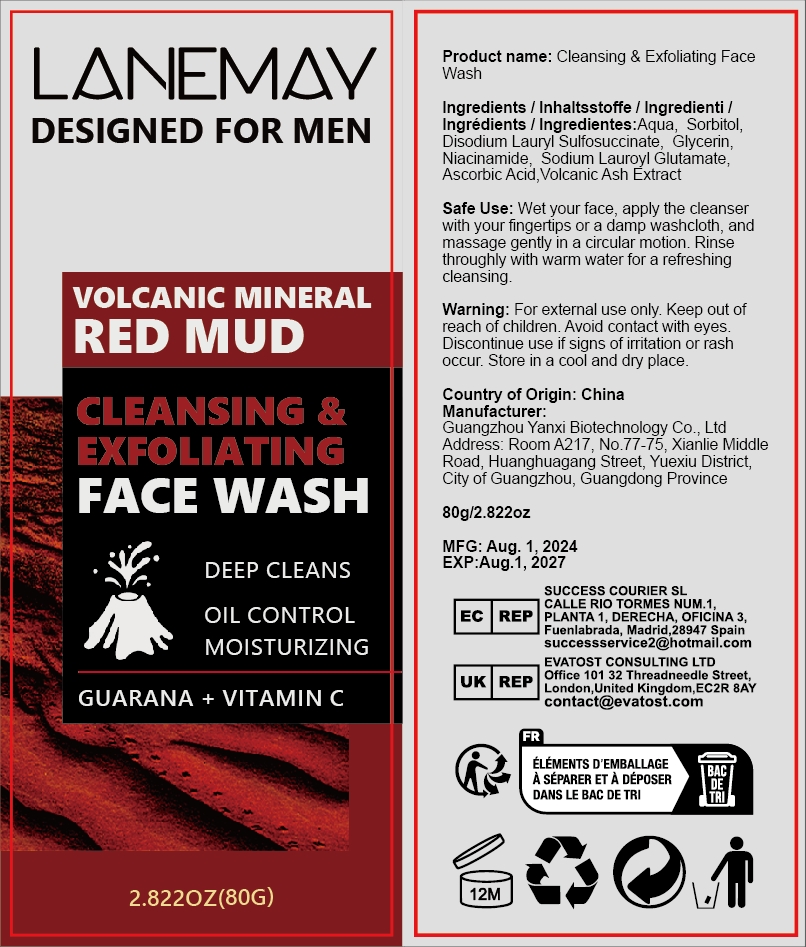 DRUG LABEL: cleansing  exfoliating facewash
NDC: 84025-261 | Form: CREAM
Manufacturer: Guangzhou Yanxi Biotechnology Co., Ltd
Category: otc | Type: HUMAN OTC DRUG LABEL
Date: 20241115

ACTIVE INGREDIENTS: SORBITOL 4 mg/80 g; ASCORBIC ACID 3 mg/80 g
INACTIVE INGREDIENTS: WATER

DOSAGE AND ADMINISTRATION

Wet your face, apply the cleanser with your fingertips or a damp washcloth,and massage gently in a circular motion.Rinse throughly with warm water for a refreshing cleansing.

WARNINGS

Keep out of children

INACTIVE INGREDIENT

Aqua

INDICATIONS AND USAGE

For daily skin clean

Keep out of children

PURPOSE

Deep cleans and moisturizing skin